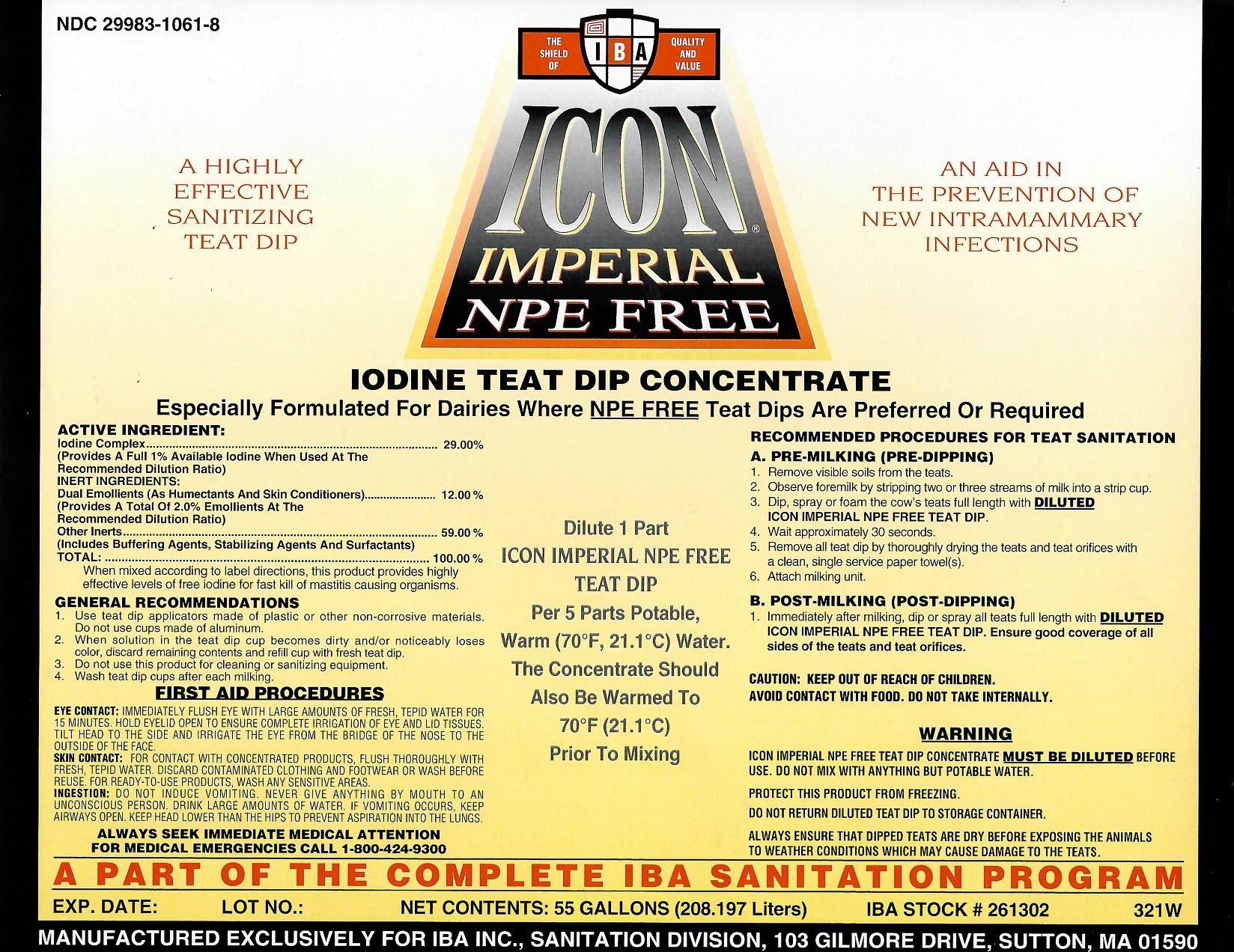 DRUG LABEL: Icon Imperial NPE Free
NDC: 29983-1061 | Form: LIQUID
Manufacturer: IBA
Category: animal | Type: OTC ANIMAL DRUG LABEL
Date: 20251202

ACTIVE INGREDIENTS: iodine 1.0 kg/100 kg

Icon Imperial NPE Free

ACTIVE INGREDIENT:

IODINE COMPLEX..........29.00%
(PROVIDES .5% available Iodine When Used At The Recommended Dilution Ratio)

INERT INGREDIENTS:

Dual Emollients (As Humectants And Skin Conditioners............................................................12.00%
(Provides A Total Of 2.0% skin conditioners at the recommended dilution ratio)
OTHER INERTS.........................................................................59.00%
(INCLUDES BUFFERING AGENTS, STABILIZING AGENTS AND SURFACTANTS)
TOTAL:.....................................................................................100.00%
When mixed according to label directions, this product provides highly effective levels of free iodine for fast kill of mastitis causing organisms.

GENERAL RECOMMENDATIONS

1. Use teat dip applicators made of plastic or other non-corrosive materials. Do not use cups made of aluminum.

2. When solution in the teat dip cup becomes dirty and/or noticeably loses color, discard remaining contents and refill cup with fresh teat dip.

3. Do not use this product for cleaning or sanitizing equipment

4. Wash Teat Dip cups after each milking.

FIRST AID PROCEDURES

EYE CONTACT: IMMEDIATELY FLUSH EYE WITH LARGE AMOUNTS OF FRESH, TEPID WATER FOR 15 MINUTES. HOLD EYELID OPEN TO ENSURE COMPLETE IRRIGATION OF EYE AND LID TISSUES. TILT HEAD TO THE SIDE AND IRRIGATE THE EYE FROM THE BRIDGE OF THE NOSE TO THE OUTSIDE OF THE FACE.

SKIN CONTACT: FOR CONTACT WITH CONCENTRATED PRODUCTS, FLUSH THOROUGHLY WITH FRESH, TEPID WATER. DISCARD CONTAMINATED CLOTHONG AND FOOTWEAR OR WASH BEFORE REUSE. FOR READY-TO-USE PRODUCTS, WASH ANY SENSITIVE AREAS.

INGESTION: DO NOT INDUCE VOMITING. NEVER GIVE ANYTHING BY MOUTH TO AN UNCONSCIOUS PERSON. DRINK LARGE AMOUNTS OF WATER. IF VOMITING OCCURS KEEP AIRWAYS OPEN. KEEP HEAD LOWER THAN THE HIPS TO PREVENT ASPIRATION INTO THE LUNGS.

ALWAYS SEEK IMMEDIATE MEDICAL ATTENTION

FOR MEDICAL EMERGENCIES CALL 1-800-424-9300

RECOMMENDED PROCEDURES FOR TEAT SANITATION

A. PRE-MILKING (PRE-DIPPING)
1. REMOVE VISIBLE SOILS FROM THE TEATS.
2. OBSERVE FOREMILK BY STRIPPING TWO OR THREE STREAMS OF MILK INTO A STRIP CUP.
3. DIP, SPRAY, OR FOAM THE COW'S TEATS FULL LENGTH WITH DILUTED ICON IMPERIAL NPE FREE TEAT DIP.
4 WAIT APPROXIMATELY 30 SECONDS.
5. REMOVE ALL TEAT DIP BY THOROUGHLY DRYING THE TEATS AND TEAT ORIFICES WITH A CLEAN, SINGLE SERVICE PAPER TOWEL(S).
6. ATTACH MILKING UNIT.
B. POST-MILKING (POST-DIPPING)
Immediately after milking dip or spray all teats full length with DILUTED ICON IMPERIAL NPE FREE TEAT DIP. Ensure good coverage of all sides of the teats and teat orifices.

Dilute 1 Part

ICON IMPERIAL NPE FREE

TEAT DIP

Per 5 Parts Potable

WARM (70 ˚ F, 21 ˚ C) WATER. THIS CONCENTRATE SHOULD ALSO BE WARMED TO (70˚F, 21˚C) PRIOR TO MIXING.

CAUTION

KEEP OUT OF REACH OF CHILDREN

CAUTION

AVOID CONTACT WITH FOOD. DO NOT TAKE INTERNALLY.

WARNING

ICON IMPERIAL NPE FREE TEAT DIP CONCENTRATE MUST BE DILUTED BEFORE USE. DO NOT MIX WITH ANYTHING WITH POTABLE WATER.

PROTECT THIS PRODUCT FROM FREEZING

DO NOT RETURN TEAT DIP LEFT IN THE TEAT DIPPER TO STORAGE CONTAINER.

ALWAYS ENSURE THAT DIPPED TEATS ARE DRY BEFORE EXPOSING THE ANIMALS TO WEATHER CONDITIONS WHICH MAY CAUSE DAMAGE TO THE TEATS.